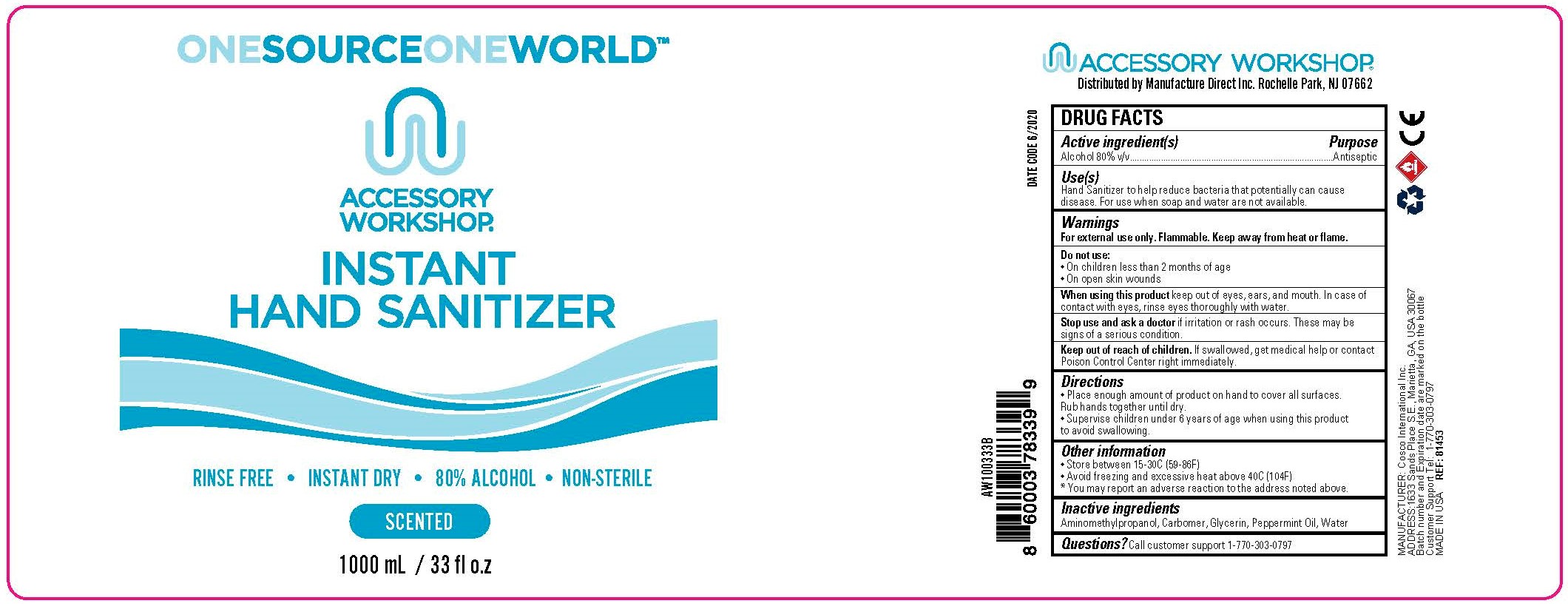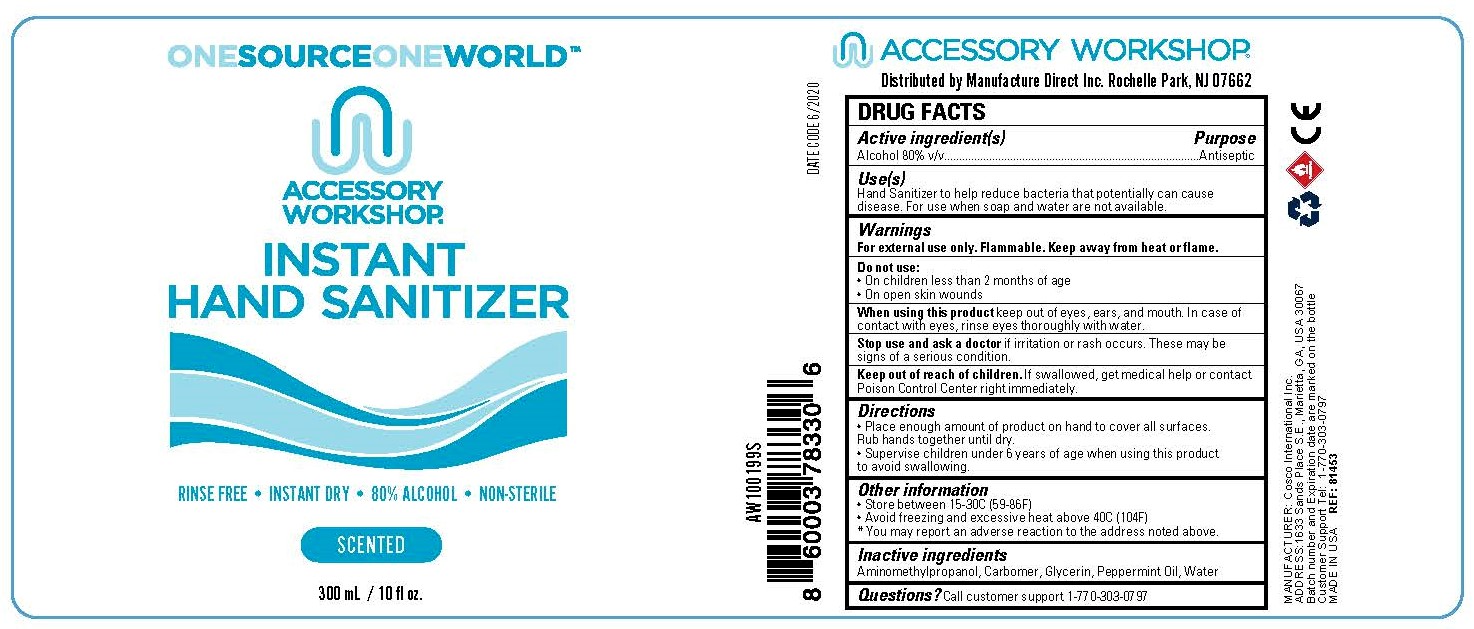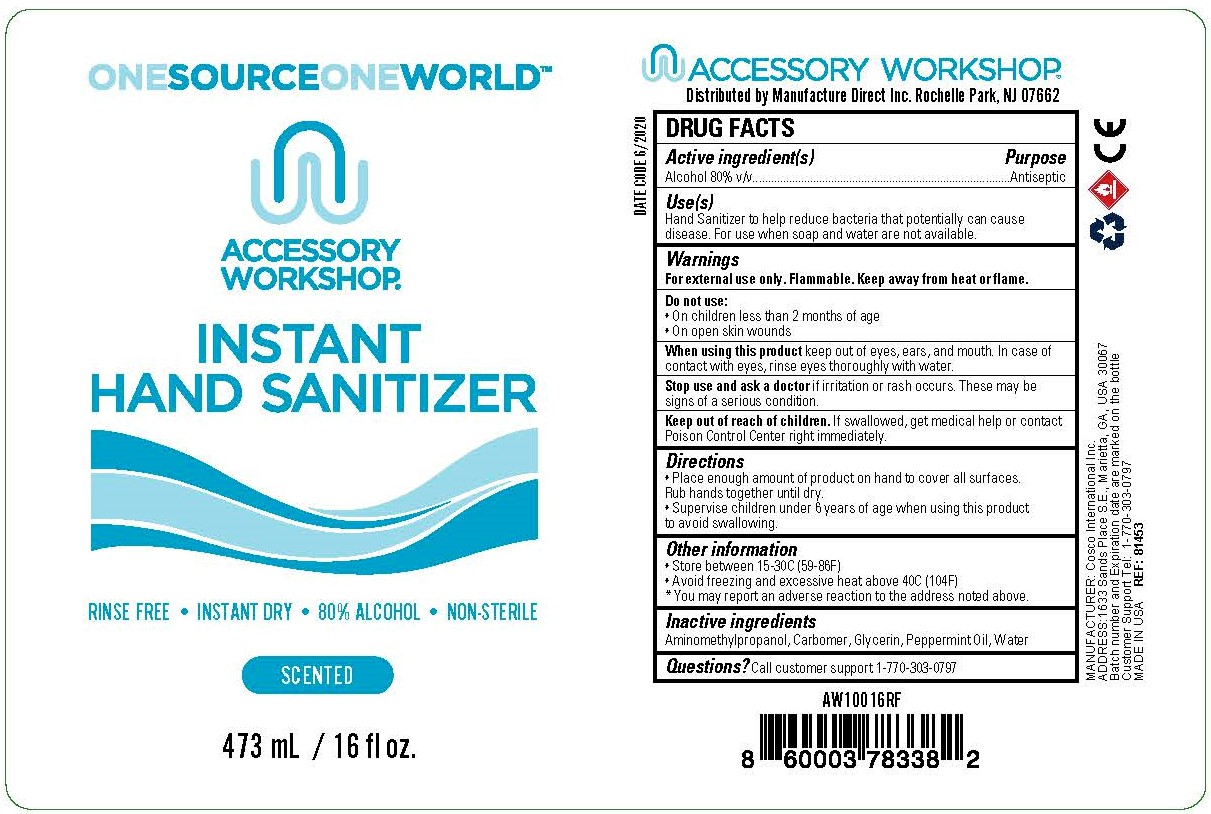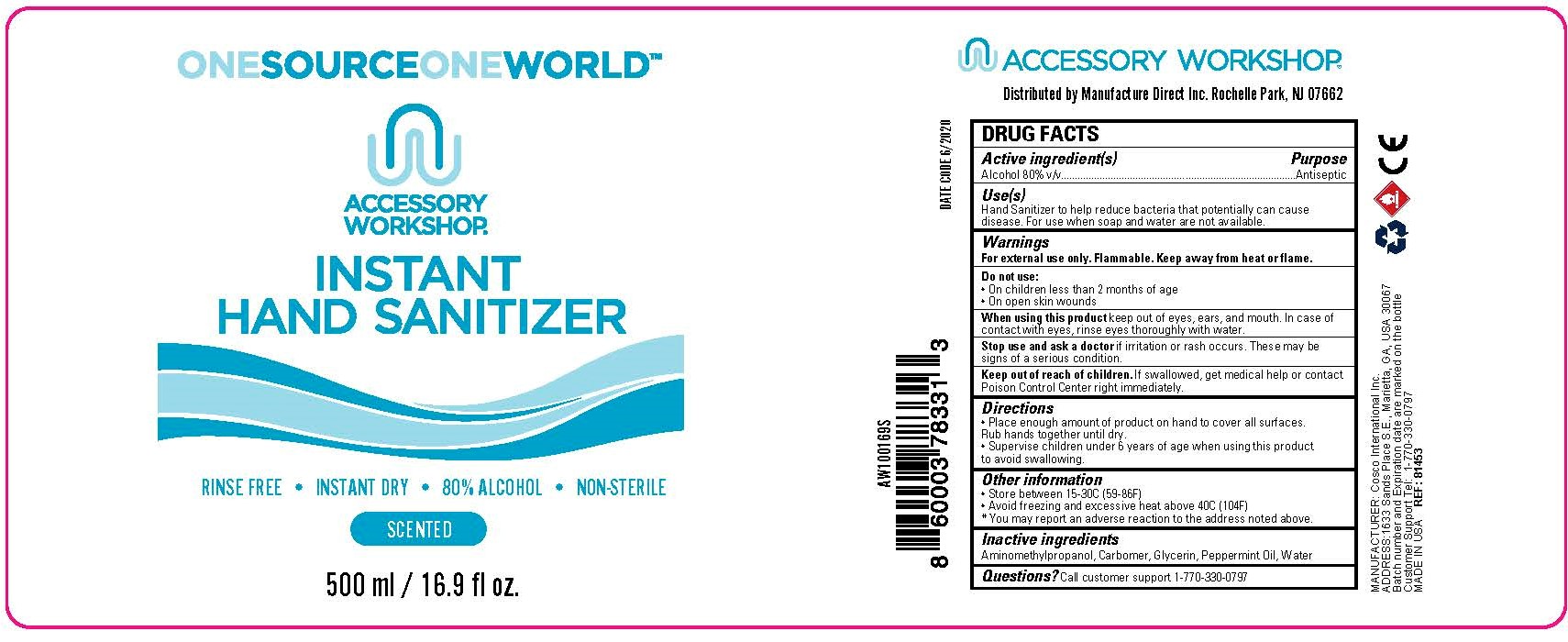 DRUG LABEL: Accessory Workshop Instant Hand Sanitizer
NDC: 52261-0006 | Form: GEL
Manufacturer: Cosco International, Inc.
Category: otc | Type: HUMAN OTC DRUG LABEL
Date: 20200615

ACTIVE INGREDIENTS: ALCOHOL 80 L/100 L
INACTIVE INGREDIENTS: GLYCERIN; AMINOMETHYLPROPANOL; CARBOMER HOMOPOLYMER, UNSPECIFIED TYPE; PEPPERMINT OIL; WATER

Active Ingredient(s)

Alcohol 80% v/v. Purpose: Antiseptic

Purpose

Antiseptic, Hand Sanitizer

Use

Hand Sanitizer to help reduce bacteria that potentially can cause disease. For use when soap and water are not available.

Warnings

For external use only. Flammable. Keep away from heat or flame

Do not use

- on children less than 2 months of age
- on open skin wounds

When using this product keep out of eyes, ears, and mouth. In case of contact with eyes, rinse eyes thoroughly with water.

Stop use and ask a doctor if irritation or rash occurs. These may be signs of a serious condition.

Keep out of reach of children. If swallowed, get medical help or contact a Poison Control Center immediately.

Directions

- Place enough product on hands to cover all surfaces. Rub hands together until dry.
- Supervise children under 6 years of age when using this product to avoid swallowing.

Other information

- Store between 15-30C (59-86F)
- Avoid freezing and excessive heat above 40C (104F)
- You may report an adverse reaction to the address noted above.

Inactive ingredients

Aminomethylpropanol, Carbomer, Glycerin, Peppermint Oil, Water